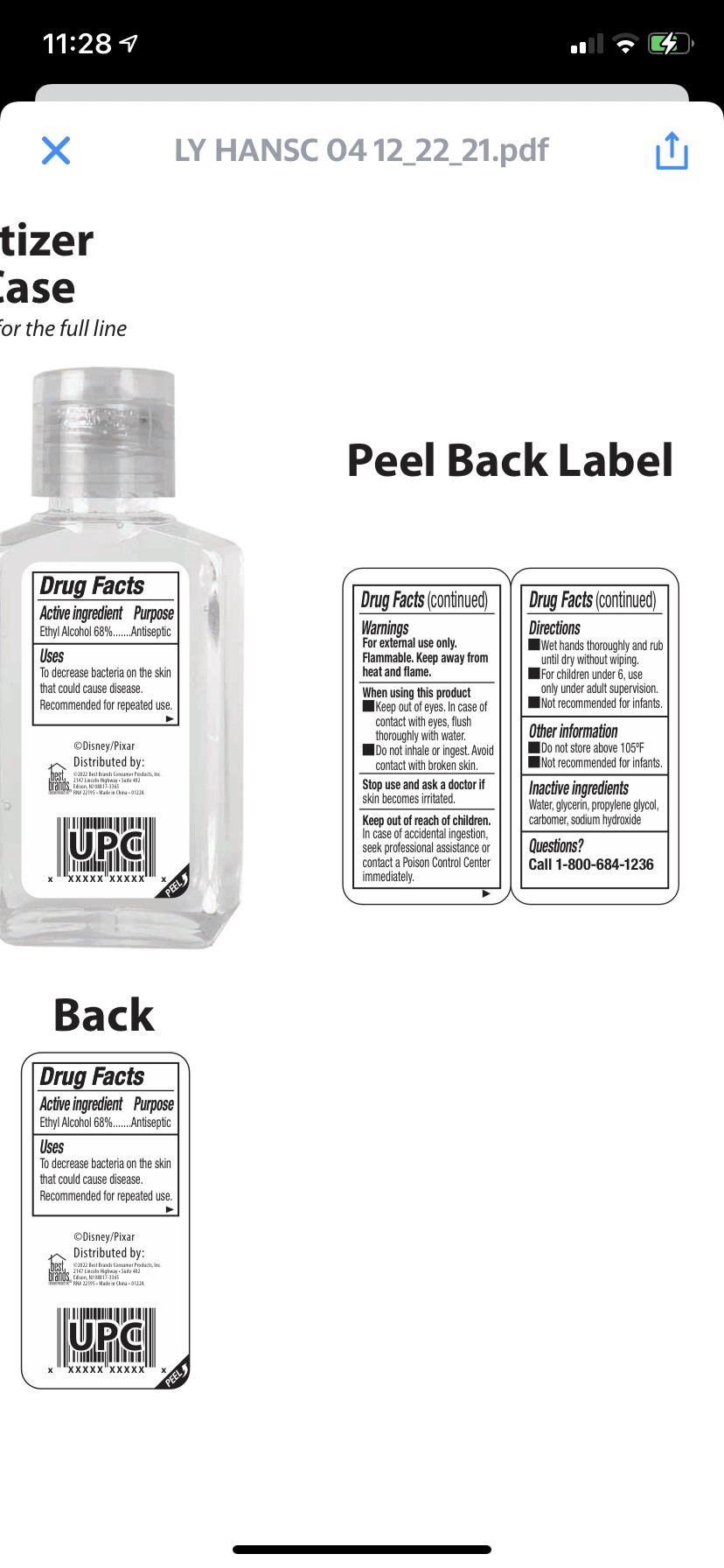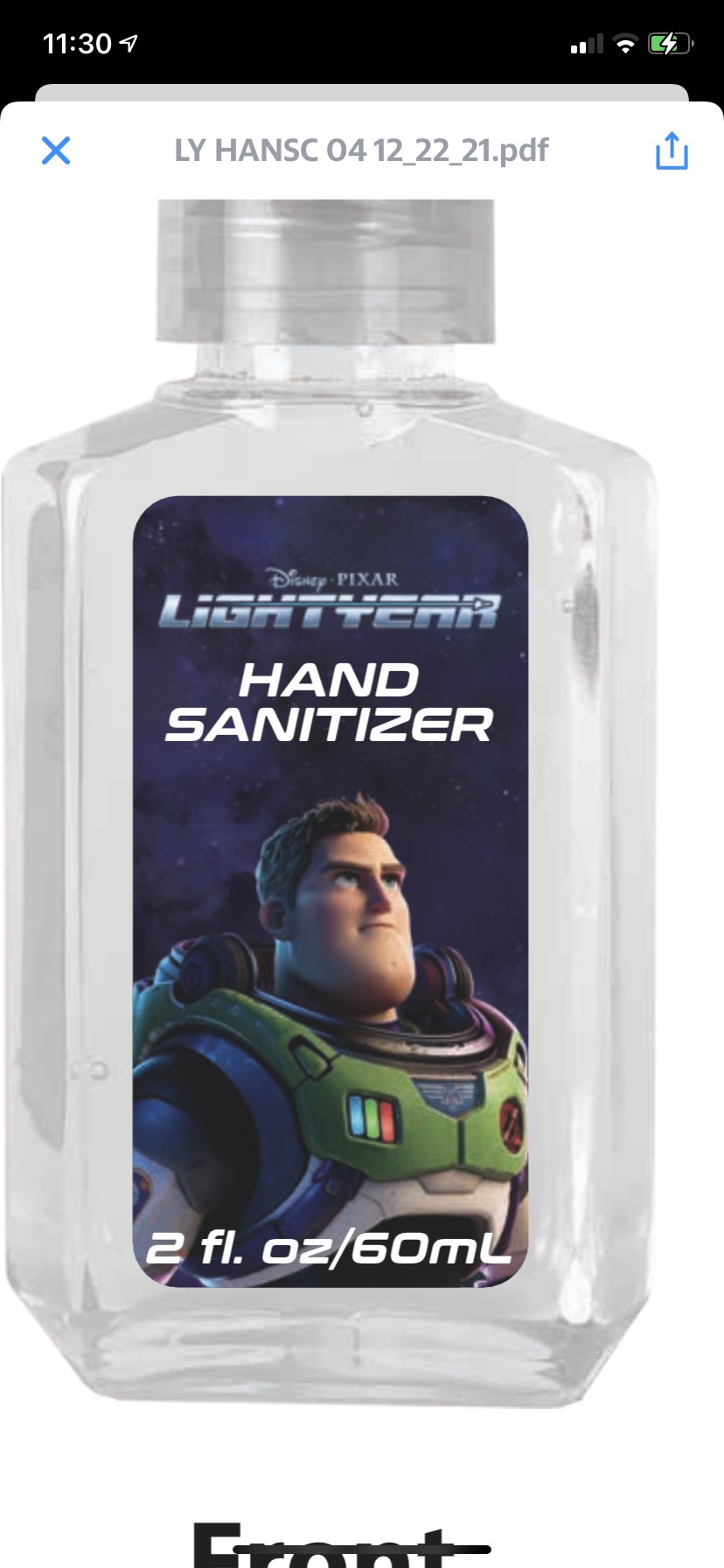 DRUG LABEL: Disney PIXAR LIGHTYEAR HAND SANITIZER
NDC: 74530-061 | Form: SOLUTION
Manufacturer: Best Brand Consumers Products, Inc.
Category: otc | Type: HUMAN OTC DRUG LABEL
Date: 20220111

ACTIVE INGREDIENTS: ALCOHOL 68 mL/100 mL
INACTIVE INGREDIENTS: GLYCERIN; SODIUM HYDROXIDE; WATER; CARBOMER 940; PROPYLENE GLYCOL

74530-061

Drug Fact

Active Ingredient(s)

Ethyl Alcohol 68%

Purpose

Antiseptic

Use

To decrease the bacteria on the skin that could cause disease

Recommended for repeated use

Warnings

For external use only.

Flammable. Keep away from heat and flame

Stop use and ask a doctor if skin becomes irritated

WHEN USING

Keep out of eyes. In case of contact with eyes, flush thoroughly with water

Do not inhale or ingest. Avoid contact with broken skin

Keep out of reach of children. In case of accidental ingestion, seek professional assitance or contact a Poison Control Center immediately.

Directions

Wet hands thoroughly with products and rub untill dry withour wiping

For children under 6, use only under adult supervision

Not recommended for infants

Other information

Do not store above 105F

Not recommended for infants

Inactive ingredients

Water, glycerin, propylene glycol, carbomer, sodium hydroxide